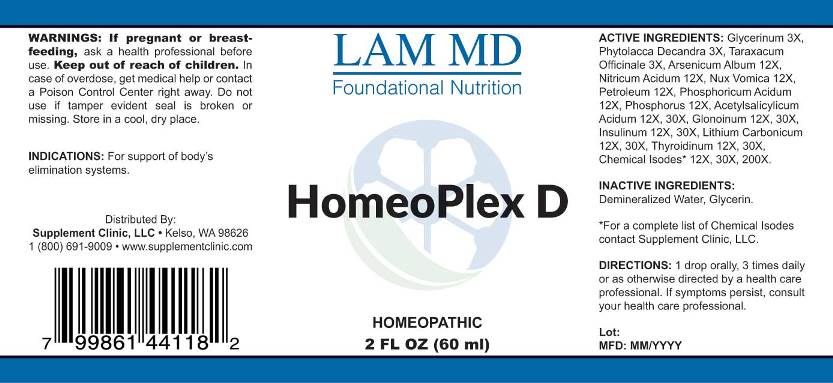 DRUG LABEL: Homeoplex D
NDC: 71781-0003 | Form: LIQUID
Manufacturer: Supplement Clinic, LLC.
Category: homeopathic | Type: HUMAN OTC DRUG LABEL
Date: 20171101

ACTIVE INGREDIENTS: GLYCERIN 3 [hp_X]/1 mL; PHYTOLACCA AMERICANA ROOT 3 [hp_X]/1 mL; TARAXACUM OFFICINALE 3 [hp_X]/1 mL; ARSENIC TRIOXIDE 12 [hp_X]/1 mL; NITRIC ACID 12 [hp_X]/1 mL; STRYCHNOS NUX-VOMICA SEED 12 [hp_X]/1 mL; KEROSENE 12 [hp_X]/1 mL; PHOSPHORIC ACID 12 [hp_X]/1 mL; PHOSPHORUS 12 [hp_X]/1 mL; ASPIRIN 12 [hp_X]/1 mL; NITROGLYCERIN 12 [hp_X]/1 mL; INSULIN PORK 12 [hp_X]/1 mL; LITHIUM CARBONATE 12 [hp_X]/1 mL; SUS SCROFA THYROID 12 [hp_X]/1 mL; SALICYLIC ACID 12 [hp_X]/1 mL; CORTICOTROPIN 12 [hp_X]/1 mL; CORTISONE ACETATE 12 [hp_X]/1 mL; EUGENOL 12 [hp_X]/1 mL; STEARYL ALCOHOL 12 [hp_X]/1 mL; XYLITOL 12 [hp_X]/1 mL; ESTRONE 12 [hp_X]/1 mL; BENZOIC ACID 12 [hp_X]/1 mL; CHLORINE 12 [hp_X]/1 mL; POTASSIUM SORBATE 12 [hp_X]/1 mL; SORBITOL 12 [hp_X]/1 mL; RESORCINOL 12 [hp_X]/1 mL; BENZYL ALCOHOL 12 [hp_X]/1 mL; LACTIC ACID, DL- 12 [hp_X]/1 mL; ISOPROPYL PALMITATE 12 [hp_X]/1 mL; BORIC ACID 12 [hp_X]/1 mL; ACETIC ACID 12 [hp_X]/1 mL; PHENYLBUTAZONE 12 [hp_X]/1 mL; PETROLATUM 12 [hp_X]/1 mL; LEAD 12 [hp_X]/1 mL
INACTIVE INGREDIENTS: WATER

Drug Facts:

ACTIVE INGREDIENTS:

Glycerinum 3X, Phytolacca Decandra 3X, Taraxacum Officinale 3X, Arsenicum Album 12X, Nitricum Acidum 12X, Nux Vomica 12X, Petroleum 12X, Phosphoricum Acidum 12X, Phosphorus 12X, Acetylsalicylicum Acidum 12X, 30X, Glonoinum 12X, 30X, Insulinum (Suis) 12X, 30X, Lithium Carbonicum 12X, 30X, Thyroidinum (Suis) 12X, 30X, Salicylicum Acidum 12X, 30X, 200X, Adrenocorticotrophin 12X, 30X, 200X, Cortisone Aceticum 12X, 30X, 200X, Eugenol 12X, 30X, 200X, Stearyl Alcohol 12X, 30X, 200X, Xylitol 12X, 30X, 200X, Folliculinum 12X, 30X, 200X, Benzoicum Acidum 12X, 30X, 200X, Chlorinum 12X, 30X, 200X, Potassium Sorbate 12X, 30X, 200X, Sorbitol 12X, 30X, 200X, Resorcinum 12X, 30X, 200X, Benzyl Alcohol 12X, 30X, 200X, Lacticum Acidum 12X, 30X, 200X, Isopropyl Palmitate 12X, 30X, 200X, Boricum Acidum 12X, 30X, 200X, Aceticum Acidum 12X, 30X, 200X, Phenyl Butazone 12X, 30X, 200X, Petroleum Jelly 12X, 30X, 200X, Plumbum Metallicum 12X, 30X, 200X.

INDICATIONS:

For support of body's elimination systems.

WARNINGS:

If pregnant or breastfeeding, ask a health professional before use.
Keep out of reach of children. In case of overdose, get medical help or contact a Poison Control Center right away.
Do not use if tamper evident seal is broken or missing.
Store in a cool, dry place.

Keep out of reach of children. In case of overdose, get medical help or contact a Poison Control Center right away.

DIRECTIONS:

1 drop orally, 3 times daily or as otherwise directed by a health care professional. If symptoms persist, consult your health care professional.

INDICATIONS:

For support of body's elimination systems.

INACTIVE INGREDIENTS:

Demineralized Water, Glycerin

QUESTIONS:

Distributed By:
Supplement Clinic, LLC. • Kelso, WA 98626
1(800)691-9009 • www.supplementclinic.com

PACKAGE LABEL DISPLAY:

LAM MD
Foundational Nutrition

HomeoPlex D

HOMEOPATHIC
2 FL OZ (60 ml)